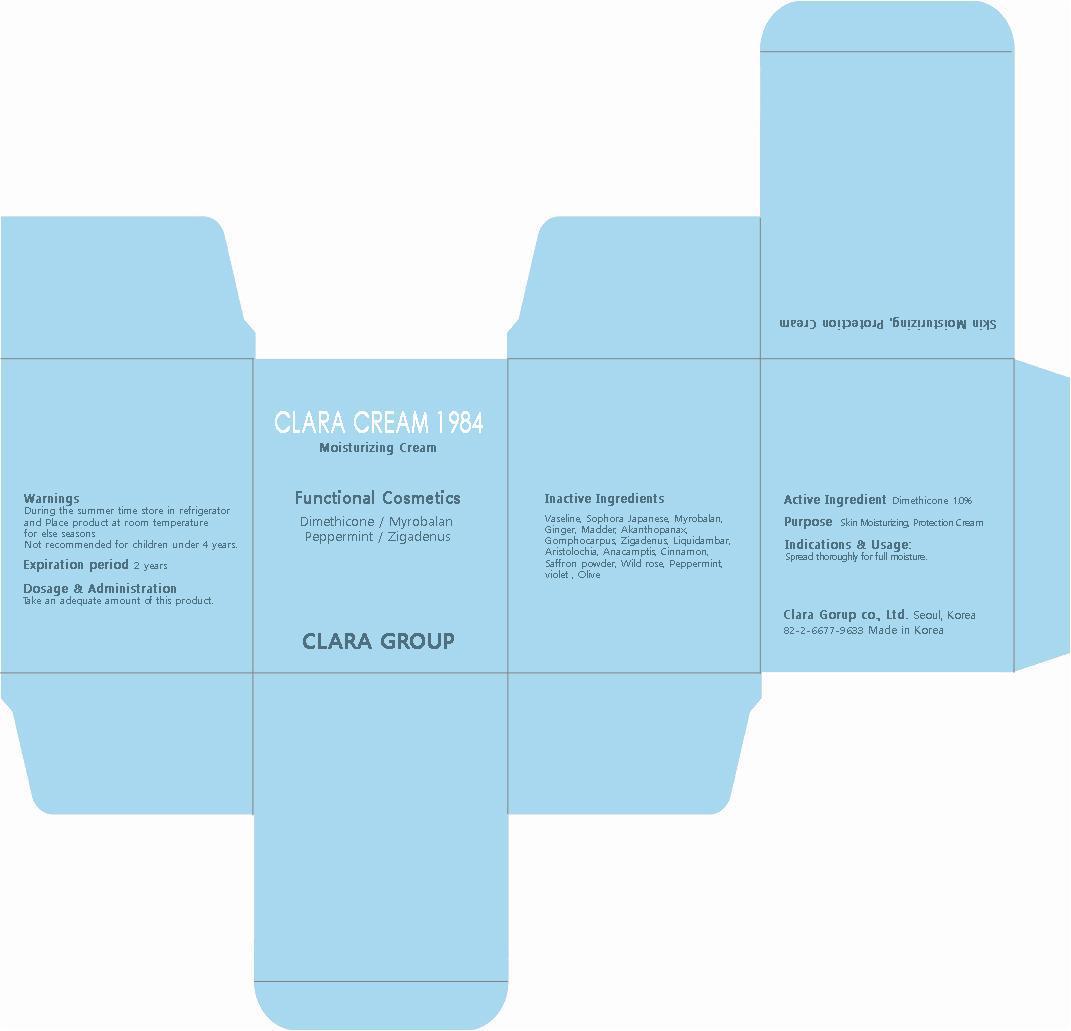 DRUG LABEL: CLARA 1984
NDC: 69404-010 | Form: CREAM
Manufacturer: CLARA GROUP
Category: otc | Type: HUMAN OTC DRUG LABEL
Date: 20150109

ACTIVE INGREDIENTS: DIMETHICONE 0.5 mg/50 mL
INACTIVE INGREDIENTS: Cinnamon

ACTIVE INGREDIENT

Active Ingredient: DIMETHICONE 1.0%

INACTIVE INGREDIENT

Inactive Ingredients:
Vaseline, Sophora Japanese, Myrobalan, Ginger, Madder, Akanthopanax, Gomphocarpus, Zigadenus, Liquidambar, Aristolochia, Anacamptis, Cinnamon, Saffron powder, Wild rose, Peppermint, violet , Olive

PURPOSE

Purpose: Skin Moisturizing, Protection

WARNINGS

During the summer time store in refrigerator. and Place product at room temperature for else seasons. /
Not recommended for children under 4 years. / Expiration period: 2 years

KEEP OUT OF REACH OF CHILDREN

Not recommended for children under 4 years.

INDICATIONS & USAGE

Indications and Usage:
Spread thoroughly for full moisture.

DOSAGE & ADMINISTRATION

Dosage and Administration:
Take an adequate amount of this product.